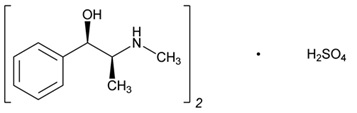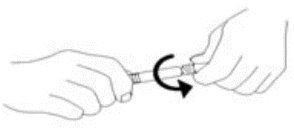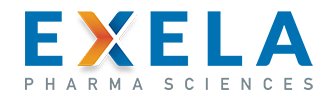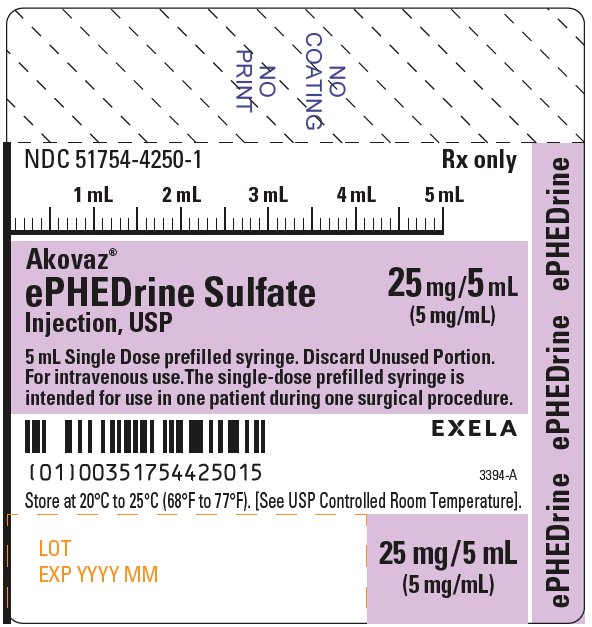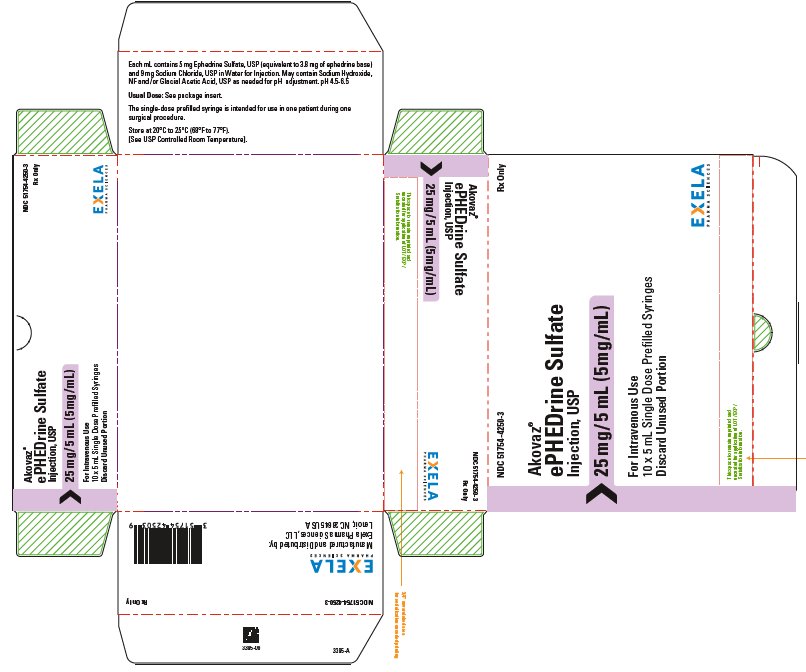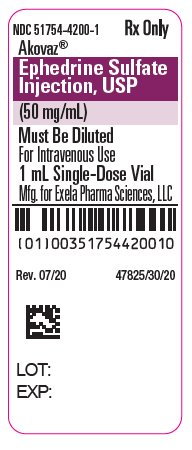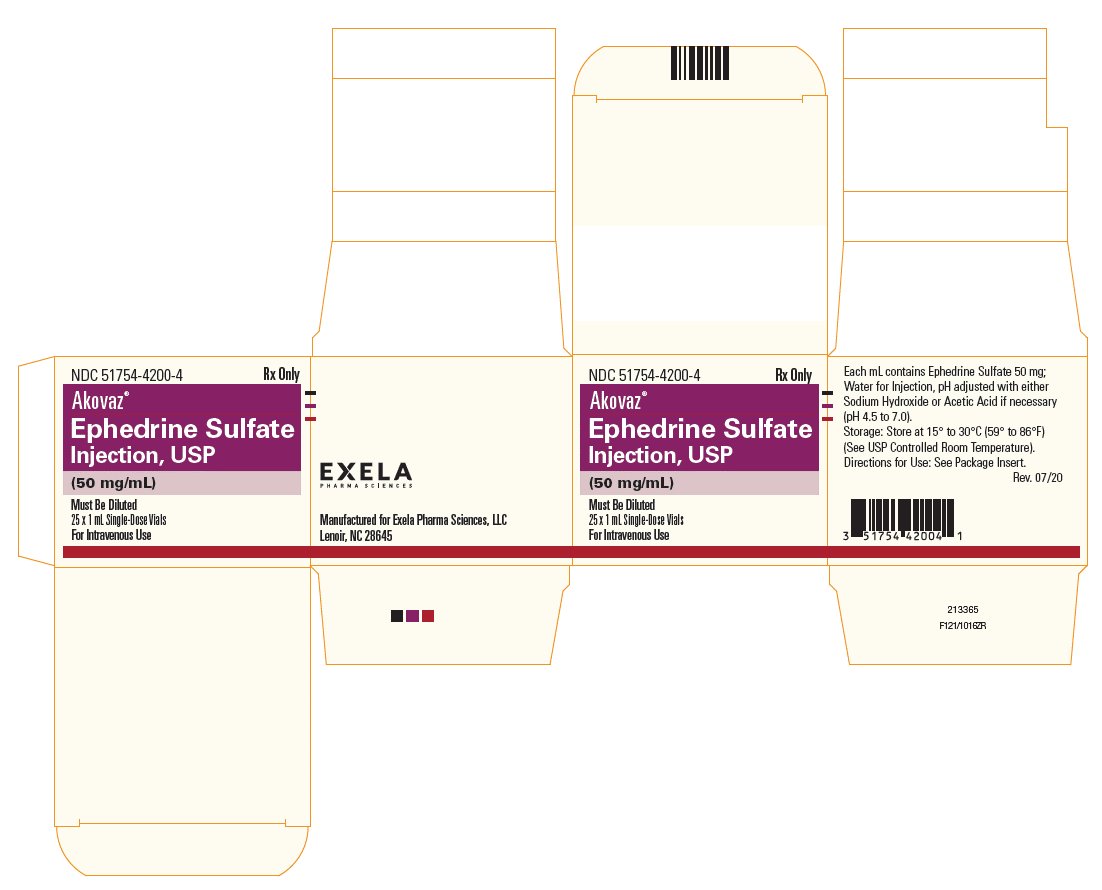 DRUG LABEL: Akovaz
NDC: 51754-4200 | Form: INJECTION
Manufacturer: Exela Pharma Sciences, LLC
Category: prescription | Type: HUMAN PRESCRIPTION DRUG LABEL
Date: 20201127

ACTIVE INGREDIENTS: EPHEDRINE SULFATE 50 mg/1 mL
INACTIVE INGREDIENTS: WATER; ACETIC ACID; SODIUM HYDROXIDE

HIGHLIGHTS OF PRESCRIBING INFORMATION

These highlights do not include all the information needed to use AKOVAZ® safely and effectively. See full prescribing information for AKOVAZ.
AKOVAZ (ephedrine sulfate injection) for intravenous use
Initial U.S. Approval: 2016

1 INDICATIONS AND USAGE

AKOVAZ injection is an alpha- and beta-adrenergic agonist and a norepinephrine-releasing agent that is indicated for the treatment of clinically important hypotension occurring in the setting of anesthesia. (1)

2 DOSAGE AND ADMINISTRATION

- Should be administered by trained healthcare providers (2.1)
- AKOVAZ injection, 50 mg/mL, must be diluted before administration as an intravenous bolus dose. (2.1)
- AKOVAZ injection, 5 mg/mL in a pre-filled syringe, is a premixed formulation. Do not dilute prior to use. (2.1)
- Bolus intravenous injection: 5 mg to 10 mg as needed, not to exceed 50 mg. (2.1)

3 DOSAGE FORMS AND STRENGTHS

Injection: 50 mg/mL ephedrine sulfate in single-dose vial and 25 mg/5 mL (5 mg/mL) ephedrine sulfate in a 5 mL single-dose prefilled syringe (3)

4 CONTRAINDICATIONS

None (4)

5 WARNINGS AND PRECAUTIONS

- Pressor Effects with Concomitant Use with Oxytocic Drugs: Pressor effect of sympathomimetic pressor amines is potentiated (5.1)
- Tachyphylaxis and Tolerance: Repeated administration of ephedrine may cause tachyphylaxis (5.2)

6 ADVERSE REACTIONS

Most common adverse reactions during treatment: nausea, vomiting, and tachycardia. (6)

To report SUSPECTED ADVERSE REACTIONS, contact Exela Pharma Sciences, LLC at 1-888-451-4321 or FDA at 1-800-FDA-1088 or www.fda.gov/medwatch.

7 DRUG INTERACTIONS

- Interactions that Augment Pressor Effect: clonidine, oxytocin and oxytocic drugs, propofol, monoamine oxidase inhibitors (MAOIs), and atropine. Monitor blood pressure. (7)
- Interactions that Antagonize the Pressor Effect: Antagonistic effects with α-adrenergic antagonists, β-adrenergic antagonists, reserpine, quinidine, mephentermine. Monitor blood pressure. (7)
- Guanethidine: Ephedrine may inhibit the neuron blockage produced by guanethidine, resulting in loss of antihypertensive effectiveness. Monitor blood pressure and adjust the dosage of pressor accordingly.
- Rocuronium: Ephedrine may reduce the onset time of neuromuscular blockade when used for intubation with rocuronium if administered simultaneously with anesthetic induction. Be aware of this potential interaction. No treatment or other interventions are needed.
- Epidural anesthesia: Ephedrine may decrease the efficacy of epidural blockade by hastening the regression of sensory analgesia. Monitor and treat the patient according to clinical practice.
- Theophylline: Concomitant use of ephedrine may increase the frequency of nausea, nervousness, and insomnia. Monitor patient for worsening symptoms and manage symptoms according to clinical practice.
- Cardiac glycosides: Giving ephedrine with a cardiac glycoside, such as digitalis, may increase the possibility of arrhythmias. Carefully monitor patients on cardiac glycosides who are also administered ephedrine.

FULL PRESCRIBING INFORMATION

1 INDICATIONS AND USAGE

AKOVAZ (ephedrine sulfate injection) is indicated for the treatment of clinically important hypotension occurring in the setting of anesthesia.

2 DOSAGE AND ADMINISTRATION

2.1 General Dosage and Administration Instructions

AKOVAZ (ephedrine sulfate injection), 50 mg/mL must be diluted before administration as an intravenous bolus to achieve the desired concentration. Dilute with normal saline or 5% dextrose in water.

AKOVAZ (ephedrine sulfate injection), 25 mg/5 mL (5 mg/mL) in a prefilled syringe, is a premixed formulation. Do not dilute prior to use. The single-dose prefilled syringe is intended for use in one patient during one surgical procedure. Discard any unused portion.

Inspect parenteral drug products visually for particulate matter and discoloration prior to administration, whenever solution and container permit.

2.2 Dosing for the Treatment of Clinically Important Hypotension in the Setting of Anesthesia

AKOVAZ should be administered by trained healthcare providers.

The recommended dosages for the treatment of clinically important hypotension in the setting of anesthesia is an initial dose of 5 mg to 10 mg administered by intravenous bolus. Administer additional boluses as needed, not to exceed a total dosage of 50 mg.

- Adjust dosage according to the blood pressure goal (i.e., titrate to effect).

2.3 Prepare a 5 mg/mL Solution for Bolus Intravenous Administration

For bolus intravenous administration, prepare a solution containing a final concentration of 5 mg/mL of AKOVAZ (ephedrine sulfate injection):

- Withdraw 50 mg (1 mL of 50 mg/mL) of AKOVAZ (ephedrine sulfate injection) and dilute with 9 mL of 5% Dextrose Injection or 0.9% Sodium Chloride Injection.
- Withdraw an appropriate dose of the 5 mg/mL solution prior to bolus intravenous administration.

2.4 Instructions for Use of Prefilled Syringe

1. Perform visual inspection on the syringe by verifying:

- Absence of syringe damage
- Absence of external particles
- Absence of internal particles
- Proper drug color
- Drug name
- Drug strength
- Fill volume
- Route of administration
- Expiration date to be sure the drug has not expired

2. Do not remove tamper evident seal. Push plunger rod slightly in to break the stopper loose while tip cap is still on.

3. Remove tip cap and tamper evident seal by twisting off. (See Figure 1):

Figure 1.

4. Discard the tip cap.

5. Expel air bubble.

6. Adjust dose into sterile material (if applicable).

7. Connect the syringe to an appropriate intravenous connection.

- Before injection, ensure that the syringe is securely attached to the needle or needleless luer access device (NLAD).

8. Depress plunger rod to deliver medication. Ensure that pressure is maintained on the plunger rod during the entire administration.

9. Remove syringe from NLAD (if applicable) and discard into appropriate receptacle.

- To prevent needle stick injuries, do not recap needle when needle is connected to syringe.

NOTE: All steps must be done sequentially

- Do not re-sterilize syringe
- Do not use this product on a sterile field
- Do not introduce any other fluid into the syringe at any time
- This product is for single dose only

3 DOSAGE FORMS AND STRENGTHS

AKOVAZ (ephedrine sulfate injection) is a clear, colorless, sterile solution for intravenous injection available as:

single-dose 1 mL vial that contains 50 mg/mL ephedrine sulfate, equivalent to 38 mg/mL of ephedrine base

single-dose 5 mL prefilled syringe that contains 25 mg/ 5 mL (5 mg/mL) ephedrine sulfate equivalent to 19 mg/5 mL (3.8 mg/mL) of ephedrine base

4 CONTRAINDICATIONS

None

5 WARNINGS AND PRECAUTIONS

5.1 Pressor Effect with Concomitant Oxytocic Drugs

Serious postpartum hypertension has been described in patients who received both a vasopressor (i.e., methoxamine, phenylephrine, ephedrine) and an oxytocic (i.e., methylergonovine, ergonovine) [see Drug Interactions (7)]. Some of these patients experienced a stroke. Carefully monitor the blood pressure of individuals who have received both ephedrine and an oxytocic.

5.2 Tolerance and Tachyphylaxis

Data indicate that repeated administration of ephedrine can result in tachyphylaxis. Clinicians treating anesthesia-induced hypotension with AKOVAZ (ephedrine sulfate injection) should be aware of the possibility of tachyphylaxis and should be prepared with an alternative pressor to mitigate unacceptable responsiveness.

5.3 Risk of Hypertension When Used Prophylactically

When used to prevent hypotension, ephedrine has been associated with an increased incidence of hypertension compared with when ephedrine is used to treat hypotension.

6 ADVERSE REACTIONS

The following adverse reactions associated with the use of ephedrine sulfate were identified in the literature. Because these reactions are reported voluntarily from a population of uncertain size, it is not always possible to estimate their frequency reliably or to establish a causal relationship to drug exposure.

Gastrointestinal disorders: Nausea, vomiting

Cardiac disorders: Tachycardia, palpitations (thumping heart), reactive hypertension, bradycardia, ventricular ectopics, R-R variability

Nervous system disorders: Dizziness

Psychiatric disorders: Restlessness

7 DRUG INTERACTIONS

Interactions that Augment the Pressor Effect
Oxytocin and oxytocic drugs
Clinical Impact: | Serious postpartum hypertension has been described in patients who received both a vasopressor (i.e., methoxamine, phenylephrine, ephedrine) and an oxytocic (i.e., methylergonovine, ergonovine). Some of these patients experienced a stroke.
Intervention: | Carefully monitor the blood pressure of individuals who have received both ephedrine and an oxytocic.
Clonidine, propofol, monoamine oxidase inhibitors (MAOIs), atropine
Clinical Impact: | These drugs augment the pressor effect of ephedrine.
Intervention: | Carefully monitor the blood pressure of individuals who have received both ephedrine and any of these drugs.
Interactions that Antagonize the Pressor Effect
Clinical Impact: | These drugs antagonize the pressor effect of ephedrine.
Intervention: | Carefully monitor the blood pressure of individuals who have received both ephedrine and any of these drugs.
Examples: | α-adrenergic antagonists, β-adrenergic receptor antagonists, reserpine, quinidine, mephentermine
Other Drug Interactions
Guanethidine
Clinical Impact: | Ephedrine may inhibit the neuron blockage produced by guanethidine, resulting in loss of antihypertensive effectiveness.
Intervention: | Clinician should monitor patient for blood pressor response and adjust the dosage or choice of pressor accordingly.
Rocuronium
Clinical Impact: | Ephedrine may reduce the onset time of neuromuscular blockade when used for intubation with rocuronium if administered simultaneously with anesthetic induction.
Intervention: | Be aware of this potential interaction. No treatment or other interventions are needed.
Epidural anesthesia
Clinical Impact: | Ephedrine may decrease the efficacy of epidural blockade by hastening the regression of sensory analgesia.
Intervention: | Monitor and treat the patient according to clinical practice.
Theophylline
Clinical Impact: | Concomitant use of ephedrine may increase the frequency of nausea, nervousness, and insomnia.
Intervention: | Monitor patient for worsening symptoms and manage symptoms according to clinical practice.
Cardiac glycosides
Clinical Impact: | Giving ephedrine with a cardiac glycoside, such as digitalis, may increase the possibility of arrhythmias.
Intervention: | Carefully monitor patients on cardiac glycosides who are also administered ephedrine.

8 USE IN SPECIFIC POPULATIONS

8.1 Pregnancy

Risk Summary

Available data from randomized studies, case series, and reports of ephedrine sulfate use in pregnant women have not identified a drug-associated risk of major birth defects, miscarriage, or adverse maternal or fetal outcomes. However, there are clinical considerations due to underlying conditions (see Clinical Considerations). In animal reproduction studies, decreased fetal survival and fetal body weights were observed in the presence of maternal toxicity after normotensive pregnant rats were administered 60 mg/kg intravenous ephedrine sulfate (12 times the maximum recommended human dose (MRHD) of 50 mg/day). No malformations or embryofetal adverse effects were observed when pregnant rats or rabbits were treated with intravenous bolus doses of ephedrine sulfate during organogenesis at doses 1.9 and 7.7 times the MRHD, respectively [see data].

The estimated background risk of major birth defects and miscarriage for the indicated population are unknown. All pregnancies have a background risk of birth defect, loss, or other adverse outcomes. In the U.S. general population, the estimated background risk of major birth defects and miscarriage in clinically recognized pregnancies is 2-4% and 15-20%, respectively.

Clinical Considerations

Disease-associated maternal and/or embryofetal risk

Untreated hypotension associated with spinal anesthesia for cesarean section is associated with an increase in maternal nausea and vomiting. A decrease in uterine blood flow due to maternal hypotension may result in fetal bradycardia and acidosis.

Fetal/Neonatal Adverse Reactions

Cases of potential metabolic acidosis in newborns at delivery with maternal ephedrine exposure have been reported in the literature. These reports describe umbilical artery pH of ≤7.2 at the time of delivery [see Clinical Pharmacology (12.3)]. Monitoring of the newborn for signs and symptoms of metabolic acidosis may be required. Monitoring of infant’s acid-base status is warranted to ensure that an episode of acidosis is acute and reversible.

Data

Animal Data

Decreased fetal body weights were observed when pregnant rats were administered intravenous bolus doses of 60 mg/kg ephedrine sulfate (12 times the maximum recommended human dose (MRHD) of 50 mg based on body surface area) from Gestation Day 6-17. This dose was associated with evidence of maternal toxicity (decreased body weight of dams and abnormal head movements). No malformations or fetal deaths were noted at this dose. No effects on fetal body weight were noted at 10 mg/kg (1.9 times the MRHD of 50 mg).

No evidence of malformations or embryo-fetal toxicity were noted in pregnant rabbits administered intravenous bolus doses up to 20 mg/kg ephedrine sulfate (7.7 times the maximum recommended human dose (MRHD) of 50 mg based on body surface area) from Gestation Day 6-20. This dose was associated with expected pharmacological maternal effects (increased respiration rate, dilated pupils, piloerection).

Decreased fetal survival and body weights in the presence of maternal toxicity (increased mortality) were noted when pregnant dams were administered intravenous bolus doses of 60 mg/kg epinephrine sulfate (approximately 12 times the MRHD based on body surface area) from GD 6 through Lactation Day 20. No adverse effects were noted at 10 mg/kg (1.9 times the MRHD).

8.2 Lactation

Risk Summary

A single published case report indicates that ephedrine is present in human milk. However, no information is available on the effects of the drug on the breastfed infant or the effects of the drug on milk production. The developmental and health benefits of breastfeeding should be considered along with the mother's clinical need for AKOVAZ (ephedrine sulfate injection) and any potential adverse effects on the breastfed child from AKOVAZ (ephedrine sulfate injection) or from the underlying maternal condition.

8.3 Pediatric Use

The safety and effectiveness of AKOVAZ in pediatric patients have not been established.

Animal Toxicity Data

In a study in which juvenile rats were administered intravenous bolus doses of 2, 10, or 60 mg/kg ephedrine sulfate daily from Postnatal Day 35 to 56, an increased incidence of mortality was noted at the high dose of 60 mg/kg. The no-adverse-effect level was 10 mg/kg (approximately 1.9 times a maximum daily dose of 50 mg in a 60 kg person based on body surface area).

8.4 Geriatric Use

Clinical studies of ephedrine did not include sufficient numbers of subjects aged 65 and over to determine whether they respond differently from younger subjects. Other reported clinical experience has not identified differences in responses between the elderly and younger patients. In general, dose selection for an elderly patient should be cautious, usually starting at the low end of the dosing range, reflecting the greater frequency of decreased hepatic, renal, or cardiac function, and of concomitant disease or other drug therapy. This drug is known to be substantially excreted by the kidney, and the risk of adverse reactions to this drug may be greater in patients with impaired renal function. Because elderly patients are more likely to have decreased renal function, care should be taken in dose selection, and it may be useful to monitor renal function.

8.6 Renal Impairment

Ephedrine and its metabolite are excreted in urine. In patients with renal impairment, excretion of ephedrine is likely to be affected with a corresponding increase in elimination half-life, which will lead to slow elimination of ephedrine and consequently prolonged pharmacological effect and potentially adverse reactions. Monitor patients with renal impairment carefully after the initial bolus dose for adverse events.

10 OVERDOSAGE

Overdose of ephedrine can cause a rapid rise in blood pressure. In the case of an overdose, careful monitoring of blood pressure is recommended. If blood pressure continues to rise to an unacceptable level, parenteral antihypertensive agents can be administered at the discretion of the clinician.

11 DESCRIPTION

Ephedrine is an alpha- and beta-adrenergic agonist and a norepinephrine-releasing agent. AKOVAZ (ephedrine sulfate injection) is a clear, colorless, sterile solution for intravenous injection. The chemical name of ephedrine sulfate is benzenemethanol, α-[1-(methylamino)ethyl]-, [R-(R*,S*)]-, sulfate (2:1) (salt), and the molecular weight is 428.5 g/mol. Its structural formula is depicted below:

Ephedrine sulfate is freely soluble in water and ethanol, very slightly soluble in chloroform, and practically insoluble in ether.

Each mL of the 50 mg/mL strength contains ephedrine sulfate 50 mg (equivalent to 38 mg ephedrine base) in water for injection. The pH is adjusted with sodium hydroxide and/or glacial acetic acid if necessary. The pH range is 4.5 to 7.0. The 50 mg/mL vial must be diluted before intravenous administration.

Each mL of the 5 mL single-dose prefilled syringe contains 5 mg (equivalent to 3.8 mg ephedrine base) and 9 mg Sodium Chloride, USP in Water for Injection. The pH range is 4.5 to 6.5.

12 CLINICAL PHARMACOLOGY

12.1 Mechanism of Action

Ephedrine sulfate is a sympathomimetic amine that directly acts as an agonist at α- and β-adrenergic receptors and indirectly causes the release of norepinephrine from sympathetic neurons. Pressor effects by direct alpha- and beta-adrenergic receptor activation are mediated by increases in arterial pressures, cardiac output, and peripheral resistance. Indirect adrenergic stimulation is caused by norepinephrine release from sympathetic nerves.

12.2 Pharmacodynamics

Ephedrine stimulates heart rate and cardiac output and variably increases peripheral resistance; as a result, ephedrine usually increases blood pressure. Stimulation of the α-adrenergic receptors of smooth muscle cells in the bladder base may increase the resistance to the outflow of urine. Activation of β-adrenergic receptors in the lungs promotes bronchodilation.

The overall cardiovascular effect from ephedrine is the result of a balance among α-1 adrenoceptor-mediated vasoconstriction, β-2 adrenoceptor-mediated vasoconstriction, and β-2 adrenoceptor-mediated vasodilatation. Stimulation of the β-1 adrenoceptors results in positive inotrope and chronotrope action.

Tachyphylaxis to the pressor effects of ephedrine may occur with repeated administration [see Warnings and Precautions (5.2)].

12.3 Pharmacokinetics

Publications studying pharmacokinetics of oral administration of (-)-ephedrine support that (-)-ephedrine is metabolized into norephedrine. However, the metabolism pathway is unknown. Both the parent drug and the metabolite are excreted in urine. Limited data after IV administration of ephedrine support similar observations of urinary excretion of drug and metabolite. The plasma elimination half-life of ephedrine following oral administration was about 6 hours.

Ephedrine crosses the placental barrier [see Use in Specific Populations (8.1)].

13 NONCLINICAL TOXICOLOGY

13.1 Carcinogenesis, Mutagenesis, Impairment of Fertility

Carcinogenesis: Two-year feeding studies in rats and mice conducted under the National Toxicology Program (NTP) demonstrated no evidence of carcinogenic potential with ephedrine sulfate at doses up to 10 mg/kg/day and 27 mg/kg/day (approximately 2 times and 3 times the maximum human recommended dose on a mg/m^2 basis, respectively).

Mutagenesis: Ephedrine sulfate tested negative in the in vitro bacterial reverse mutation assay, the in vitro mouse lymphoma assay, the in vitro sister chromatid exchange, the in vitro chromosomal aberration assay, and the in vivo rat bone marrow micronucleus assay.

Impairment of Fertility: There was no impact on fertility or early embryonic development in a study in which male rats were administered intravenous bolus doses of 0, 2, 10, or 60 mg/kg ephedrine sulfate (up to 12 times the maximum recommended human dose of 50 mg based on body surface area) for 28 days prior to mating and through gestation and females were treated for 14 days prior to mating through Gestation Day 7.

14 CLINICAL STUDIES

The evidence for the efficacy of ephedrine injection is derived from the published literature. Increases in blood pressure following administration of ephedrine were observed in 14 studies, including 9 where ephedrine was used in pregnant women undergoing neuraxial anesthesia during Cesarean delivery, 1 study in non-obstetric surgery under neuraxial anesthesia, and 4 studies in patients undergoing surgery under general anesthesia. Ephedrine has been shown to raise systolic and mean blood pressure when administered as a bolus dose following the development of hypotension during anesthesia.

16 HOW SUPPLIED/STORAGE AND HANDLING

AKOVAZ (ephedrine sulfate injection) is a clear, colorless, sterile solution for intravenous injection supplied as follows:

NDC | Strength | How Supplied
51754-4200-4 | 50 mg/mL of ephedrine sulfate equivalent to 38 mg/mL of ephedrine base | 1 mL clear glass vial; for single-dose (supplied in packages of 25)
51754-4250-3 | 25 mg/ 5 mL (5 mg/mL) of ephedrine sulfate equivalent to 19 mg/5 mL (3.8 mg/mL) of ephedrine base | 5 mL single-dose prefilled syringe (supplied in packages of 10)

Vial stoppers are not manufactured with natural rubber latex. Store AKOVAZ (ephedrine sulfate injection), at 25°C (77°F); excursions permitted to 15°C to 30°C (59°F to 86°F) [see USP Controlled Room Temperature]. Store in carton until time of use. For single dose only. Discard unused portion.

The single-dose 5 mL prefilled syringe is intended for use in one patient during one surgical procedure.

Manufactured for:

Exela Pharma Sciences, LLC

Lenoir, NC 28645

PRINCIPAL DISPLAY PANEL-1 mL Vial Label

NDC 51754-4200-1 Rx Only

Akovaz®

Ephedrine Sulfate

Injection, USP

(50 mg/mL)

Must Be Diluted

For Intravenous Use

1 mL Single-Dose Vial

PRINCIPAL DISPLAY PANEL – 1 ml Carton Label

NDC 51754-4200-4 Rx Only

Akovaz®

Ephedrine Sulfate

Injection, USP

(50 mg/mL)

Must Be Diluted

For Intravenous Use

25 x 1 mL Single-Dose Vials

PACKAGE/LABEL PRINCIPAL DISPLAY PANEL-5 mL Prefilled Syringe

NDC 51754-4250-1 Rx only

Akovaz

ePHEDrine Sulfate 25 mg/5 mL

Injection, USP (5 mg/mL)

5 mL Single Dose prefilled syringe. Discard Unused Portion. For intravenous use. The single-dose prefilled syringe is intended for use in one patient during one surgical procedure.

Store at 20°C to 25°C (68°F to 77°F). [See USP Controlled Room Temperature].

PACKAGE/LABEL PRINCIPAL DISPLAY PANEL-5 mL Syringe Carton

NDC 51754-4250-3 Rx only

Akovaz

ePHEDrine Sulfate

Injection, USP

25 mg/5 mL (5 mg/mL)

For Intravenous Use

10 x 5 mL Single Dose Prefilled Syringes

Discard Unused Portion.